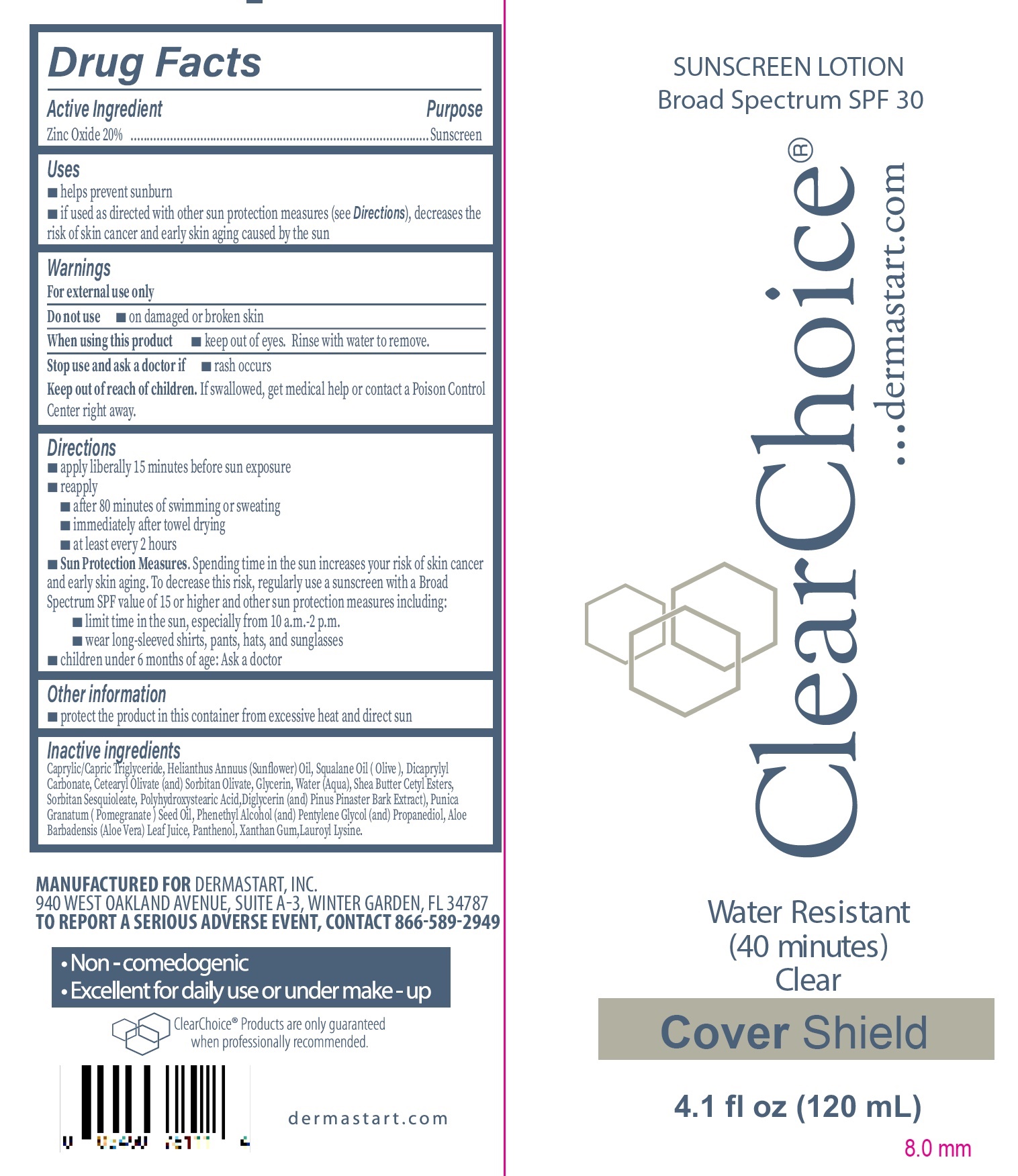 DRUG LABEL: Clear Choise Sunscreen Broad Spectrum SPF 30 Water Resistant Cover Shield
NDC: 83722-002 | Form: LOTION
Manufacturer: Dermastart Inc
Category: otc | Type: HUMAN OTC DRUG LABEL
Date: 20240207

ACTIVE INGREDIENTS: ZINC OXIDE 200 mg/1 mL
INACTIVE INGREDIENTS: MEDIUM-CHAIN TRIGLYCERIDES; HELIANTHUS ANNUUS FLOWERING TOP; GREEN OLIVE; DICAPRYLYL CARBONATE; CETEARYL OLIVATE; SORBITAN OLIVATE; GLYCERIN; WATER; SHEA BUTTER CETYL ESTERS; SORBITAN SESQUIOLEATE; DIGLYCERIN; MARITIME PINE; POMEGRANATE; PHENYLETHYL ALCOHOL; PENTYLENE GLYCOL; PROPANEDIOL; ALOE VERA LEAF; PANTHENOL; XANTHAN GUM; LAUROYL LYSINE

Clear Choise Sunscreen Lotion Broad Spectrum SPF 30 Water Resistant Cover Shield

Active Ingredient

Zinc Oxide 20%

Purpose

Sunscreen

Uses

- helps prevent sunburn
- if used as directed with other sun protection measures (see Directions), decreases the risk of skin cancer and early skin aging caused by the sun

Warnings

For external use only

Do not use

- on damaged or broken skin

When using this product

- keep out of eyes. Rinse with water to remove.

Stop use and ask a doctor if

- rash occurs

Keep out of reach of children.

If swallowed, get medical help or contact a Poison control Center right away.

Directions

- apply liberally 15 minutes before sun exposure
- reapply
- after 80 minutes of swimming or sweating
- immediately after towel drying
- at least every 2 hours
- Sun Protection Measures.Spending time in the sun increases your risk of skin cancer and early skin aging. To decrease this risk, regularly use a sunscreen with a Broad Spectrum SPF value of 15 or higher and other sun protection measures including:
- limit time in the sun, especially from 10 a.m.-2 p.m.
- wear long-sleeved shirts, pants, hats, and sunglasses
- children under 6 months of age: Ask a doctor

Other information

- protect the product in this container from excessive heat and direct sun

Inactive ingredients

Caprylic/Capric Triglyceride, Helianthus Annuus (Sunflower) Oil, Squalane Oil (Olive), Dicaprylyl Carbonate, Cetearyl Olivate (and) Sorbitan Olivate, Glycerin, Water (Aqua), Shea Butter Cetyl Esters, Sorbitan Sesquioleate, Polyhydroxystearic Acid,Diglycerin (and) Pinus Pinaster Bark Extract), Punica Granatum (Pomegranate) seed Oil, Phenethyl Alcohol (and) Pentylene Glycol (and) Propanediol, Aloe Barbadensis (Aloe Vera) Leaf Juice, Panthenol, Xanthan Gum, Lauroyl Lysine.